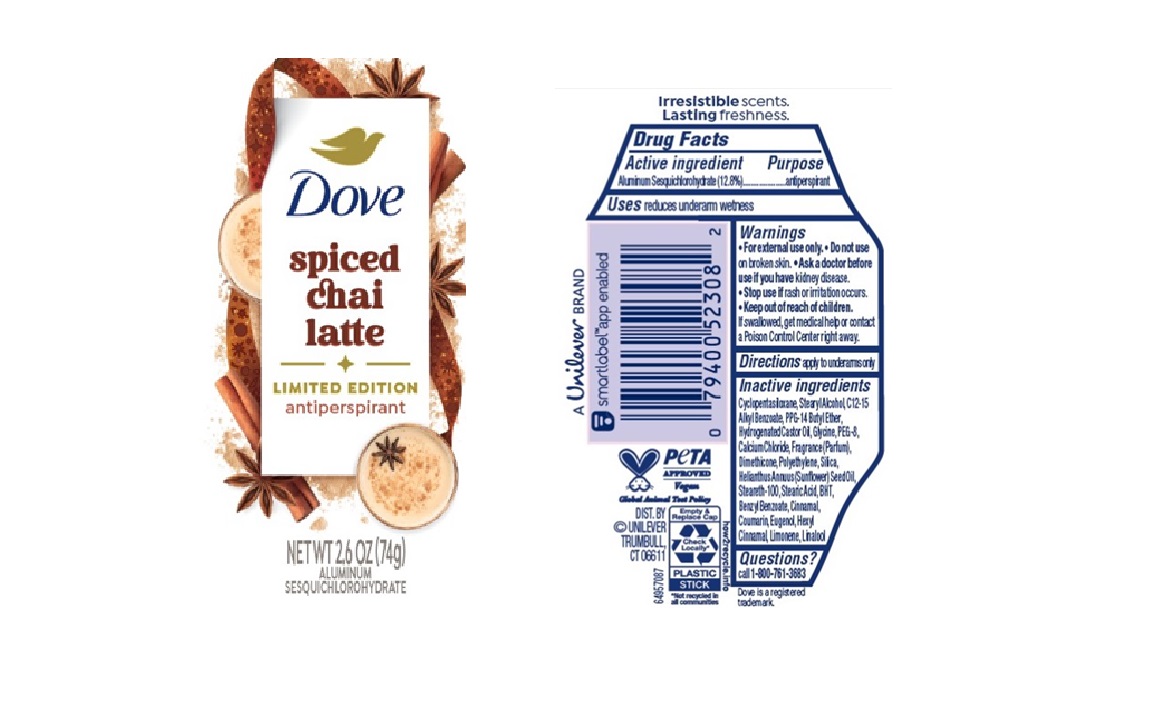 DRUG LABEL: Dove
NDC: 64942-2368 | Form: STICK
Manufacturer: Conopco d/b/a Unilever
Category: otc | Type: HUMAN OTC DRUG LABEL
Date: 20250501

ACTIVE INGREDIENTS: ALUMINUM SESQUICHLOROHYDRATE 12.8 g/100 g
INACTIVE INGREDIENTS: CINNAMAL; PEG-8; LIMONENE, (+)-; C12-15 ALKYL BENZOATE; STEARYL ALCOHOL; HYDROGENATED CASTOR OIL; SILICON DIOXIDE; POLYETHYLENE; HELIANTHUS ANNUUS (SUNFLOWER) SEED OIL; STEARETH-100; COUMARIN; EUGENOL; LINALOOL; CYCLOPENTASILOXANE; DIMETHICONE; PPG-14 BUTYL ETHER; GLYCINE; CALCIUM CHLORIDE; STEARIC ACID; BHT; BENZYL BENZOATE; HEXYL CINNAMAL

Dove Spiced Chai Latte Limited Edition Antiperspirant

DESCRIPTION

Dove Spiced Chai Latte Limited Edition Antiperspirant

ACTIVE INGREDIENT

ALUMINUM SESQUICHLOROHYDRATE (12.8%)

PURPOSE

antiperspirant

INDICATIONS AND USAGE

reduces underarm wetness

WARNINGS

For external use only.
Do not use on broken skin.
Ask a doctor before use if you have kidney disease.
Stop use if rash or irritation occurs.

Keep out of reach of children. If swallowed, get medical help or contact a Poison Control Center right away

DOSAGE AND ADMINISTRATION

apply to underarms only

INACTIVE INGREDIENT

Cyclopentasiloxane, Stearyl Alcohol, C12-15 Alkyl Benzoate, PPG-14 Butyl Ether, Hydrogenated Castor Oil, Glycine, PEG-8, Calcium Chloride, Fragrance (Parfum), Dimethicone, Polyethylene, Silica, Helianthus Annuus (Sunflower) Seed Oil, Steareth-100, Stearic Acid, BHT, Benzyl Benzoate, Cinnamal, Coumarin, Eugenol, Hexyl Cinnamal, Limonene, Linalool

QUESTIONS

Call 1-800-761-3683